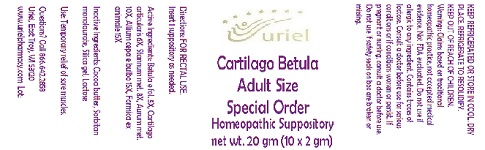 DRUG LABEL: Cartilago Betula Adult Size Special Order
NDC: 48951-3200 | Form: SUPPOSITORY
Manufacturer: Uriel Pharmacy Inc.
Category: homeopathic | Type: HUMAN OTC DRUG LABEL
Date: 20180424

ACTIVE INGREDIENTS: BETULA PUBESCENS LEAF 5 [hp_X]/1 g; BOS TAURUS CARTILAGE 6 [hp_X]/1 g; TIN 8 [hp_X]/1 g; GOLD 10 [hp_X]/1 g; ONION 15 [hp_X]/1 g; FORMICA RUFA 15 [hp_X]/1 g
INACTIVE INGREDIENTS: COCOA BUTTER; SORBITAN MONOLAURATE; SILICON DIOXIDE; LACTOSE

Cartilago Betula Adult Size Special Order

INDICATIONS AND USAGE

Directions: FOR RECTAL USE.

DOSAGE AND ADMINISTRATION

Insert 1 suppository as needed.

ACTIVE INGREDIENT

Active Ingredients: Betula e fol. 5X, Cartilago articularis 6X, Stannum met. 8X, Aurum met. 10X, Allium cepa e bulbo 15X, Formica ex animale 15X

INACTIVE INGREDIENT

Inactive Ingredients: Cocoa butter, Sorbitan monolaurate, Silica gel, Lactose

PURPOSE

Use: Temporary relief of sore muscles.

KEEP OUT OF REACH OF CHILDREN.

WARNINGS

KEEP REFRIGERATED OR STORE IN COOL, DRY PLACE. REFRIGERATE TO RESOLIDIFY.

Warnings: Claims based on traditional homeopathic practice, not accepted medical evidence. Not FDA evaluated. Do not use if allergic to any ingredient. Contains traces of lactose. Consult a doctor before use for serious conditions or if conditions worsen or persist. If pregnant or nursing, consult a doctor before use. Do not use if safety seals on box are broken or missing.

QUESTIONS

Questions? Call 866.642.2858 Uriel, East Troy, WI 53120 www.urielpharmacy.com